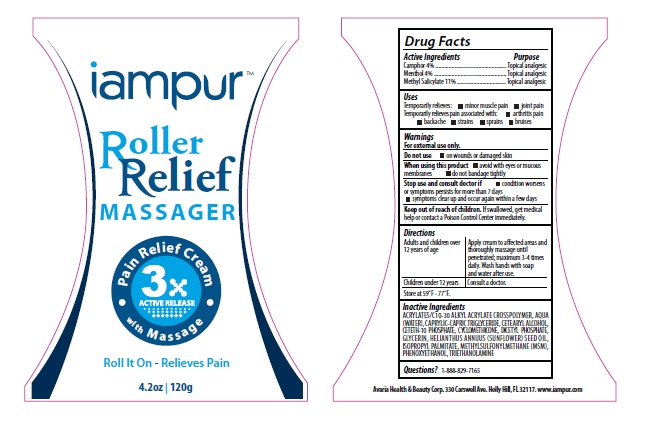 DRUG LABEL: Pain Relieving
NDC: 43493-0002 | Form: CREAM
Manufacturer: Avaria Health & Beauty Corp
Category: otc | Type: HUMAN OTC DRUG LABEL
Date: 20130524

ACTIVE INGREDIENTS: MENTHOL 4 g/1 g; CAMPHOR (NATURAL) 4 g/1 g; METHYL SALICYLATE 11 g/1 g
INACTIVE INGREDIENTS: CARBOMER INTERPOLYMER TYPE A (ALLYL SUCROSE CROSSLINKED); CETOSTEARYL ALCOHOL; CETETH-10 PHOSPHATE; DIHEXADECYL PHOSPHATE; GLUCOSAMINE SULFATE; PHENOXYETHANOL; TROLAMINE; GLYCERIN; SUNFLOWER OIL; CYCLOMETHICONE; ISOPROPYL PALMITATE; DIMETHYL SULFONE; Water

Drug Facts

ACTIVE INGREDIENT

Camphor 4%, Menthol 4%, Methyl Salicylate 11%

Uses

Temporarily relieves minor muscle pain, joint pain. Temporarily relieves pain associated with: arthritis pain, backache, strains, sprains, and bruises.

Warnings

For external use only. Use only as directed. Do not use on wounds or damaged skin. When using this product avoid contact with eyes and mucous membranes, do not bandage tightly. Stop use and consult doctor if condition worsens or symptoms persist for more than 7 days or symptoms clear up and occur again within a few days.

Directions

Adults and children 12 years of age and older: use no more than 3 to 4 times daily. Apply cream to affected areas and thoroughly massage until penetrated. Wash hands with soap and water after use.

Inactive ingredients

Acrylates C10-30 alkyl acrylate crosspolymer, Water, Caprylic/Capric Triglyceride, Cetearyl Alcohol, Ceteth-10 Phosphate, Cyclomethicone, Dicetyl Phosphate, Glycerin, Helianthus Annuus (Sunflower) Seed Oil, Isopropyl Palmitate, Methylsulfonylmethane (MSM), Phenoxyethanol, Triethanolamine.

Purpose

Topical Analgesic.

Keep out of reach of children.

If swallowed, get medical help or contact a Poison Control Center immediately.

PACKAGE LABEL

Iampur Pain Relief Massager

Pain Relieving Gel